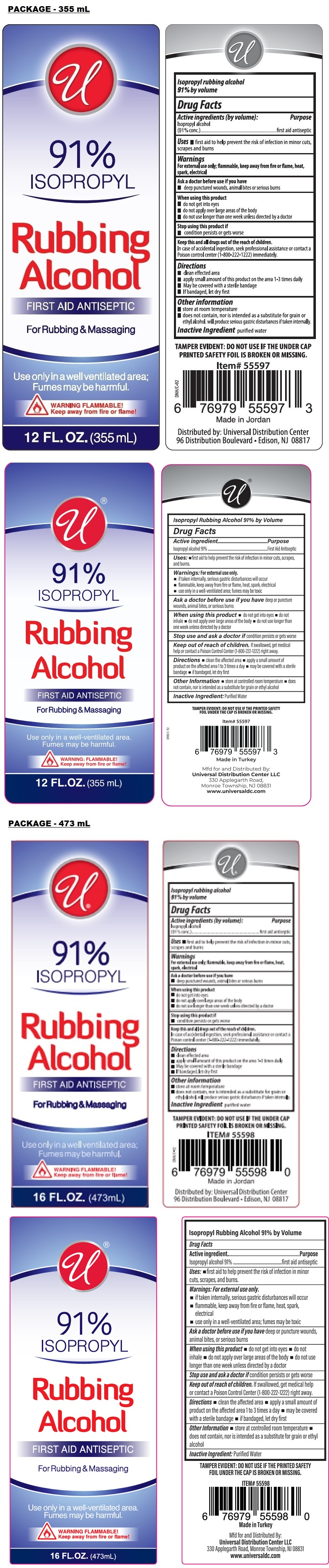 DRUG LABEL: Universal Rubbing Alcohol
NDC: 52000-406 | Form: LIQUID
Manufacturer: Universal Distribution Center LLC
Category: otc | Type: HUMAN OTC DRUG LABEL
Date: 20260223

ACTIVE INGREDIENTS: ISOPROPYL ALCOHOL 91 mL/100 mL
INACTIVE INGREDIENTS: WATER

Rubbing Alcohol

Active ingredient

Isopropyl alcohol 91%

Purpose

first aid antiseptic

Uses:

• first aid to help prevent the risk of infection in minor cuts, scrapes and burns.

Warnings:

For external use only.

• if taken internally, serious gastric disturbances will occur
• flammable, keep away from fire or flame, heat, spark, electrical
• use only in a well-ventilated area; fumes may be toxic

Ask a doctor before use if you have deep or puncture wounds, animal bites, or serious burns

When using this product • do not get into eyes • do not inhale • do not apply over large areas of the body • do not use longer than one week unless directed by a doctor

Stop use and ask a doctor if condition persists or gets worse

Keep out of reach of children. if swallowed, get medical help or contact a Poison Control Center (1‑800‑222‑1222) right away.

Directions

• clean the affected area • apply a small amount of product on the affected area 1 to 3 times a day • may be covered with a sterile bandage • If bandaged, let dry first

Other information

• store at controlled room temperature • does not contain, nor is intended as a substitute for grain or ethyl alcohol

Inactive Ingredient:

Purified Water

For Rubbing & Massaging

Use only in a well-ventilated area.
Fumes may be harmful.

TAMPER EVIDENT: DO NOT USE IF THE PRINTED SAFETY FOIL UNDER THE CAP IS BROKEN OR MISSING.

Made in Turkey

Mfd for and Distributed By:
Universal Distribution Center LLC
330 Applegarth Road, Monroe Township, NJ 08831
www.universaldc.com